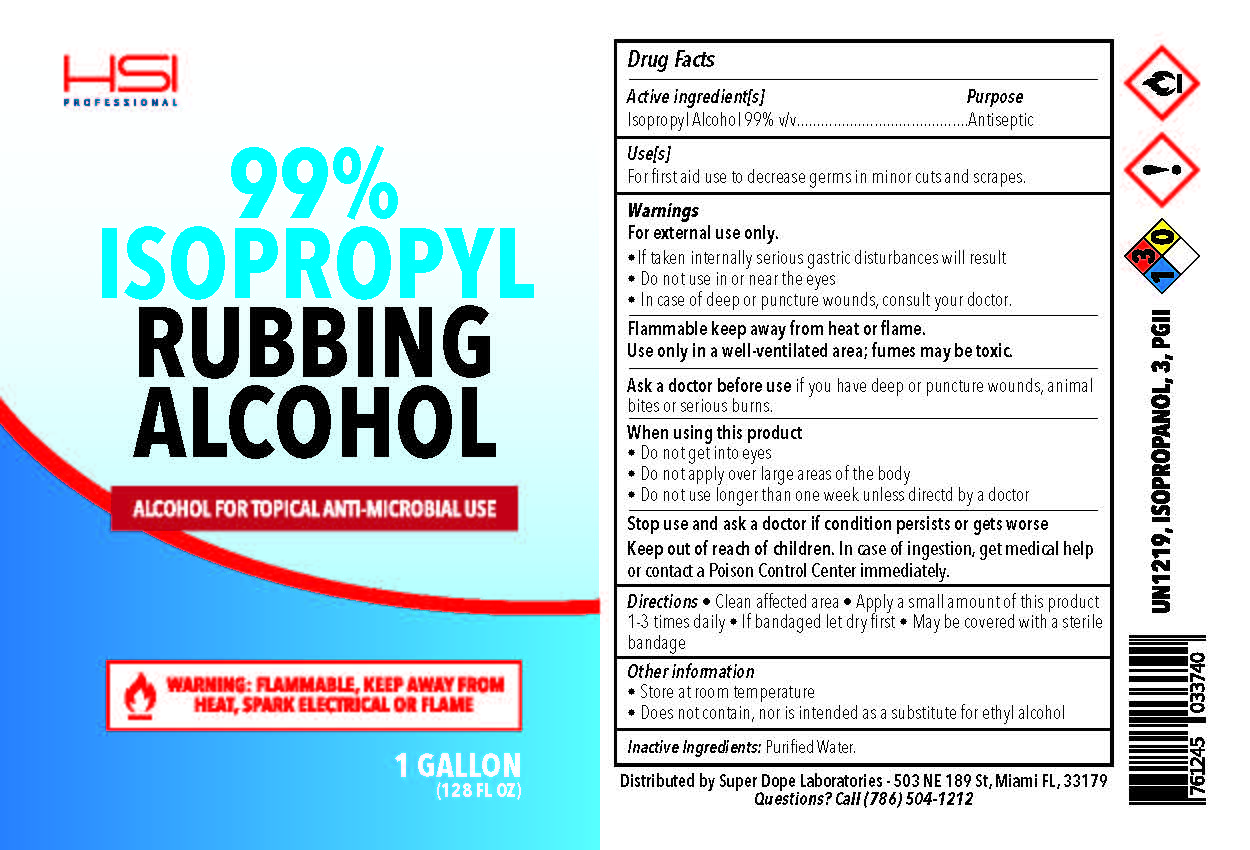 DRUG LABEL: Rubbing Alcohol
NDC: 74220-006 | Form: SOLUTION
Manufacturer: Super Dope Laboratories LLC
Category: otc | Type: HUMAN OTC DRUG LABEL
Date: 20200817

ACTIVE INGREDIENTS: ISOPROPYL ALCOHOL 99 mL/100 mL
INACTIVE INGREDIENTS: WATER

Super Dope Rubbing Alcohol

Active Ingredient(s)

Isopropyl Alcohol 99% v/v. Purpose: Antiseptic

Purpose

Antiseptic

Use

For first aid use to decrease germs in minor cuts and scrapes

Warnings

For external use only.
•If taken internally serious gastric disturbances will result
• Do not use in or near the eyes
• In case of deep or puncture wounds, consult your doctor.
Flammable keep away from heat or flame.
Use only in a well-ventilated area; fumes may be toxic.
Ask a doctor before use if you have deep or puncture wounds, animal
bites or serious burns.

When using this product
• Do not get into eyes
• Do not apply over large areas of the body
• Do not use longer than one week unless directed by a doctor

Stop use and ask a doctor if condition persists or gets worse

Keep out of reach of children. In case of ingestion, get medical help
or contact a Poison Control Center immediately.

Directions

- Directions • Clean affected area • Apply a small amount of this product
  1-3 times daily • If bandaged let dry first • May be covered with a sterile
  bandage

Other information

  • Store at room temperature
  • Does not contain, nor is intended as a substitute for ethyl alcohol

Inactive ingredients

Inactive Ingredients: Purified Water.

Package Label - Principal Display Panel

3785mL NDC: 74220-006-01